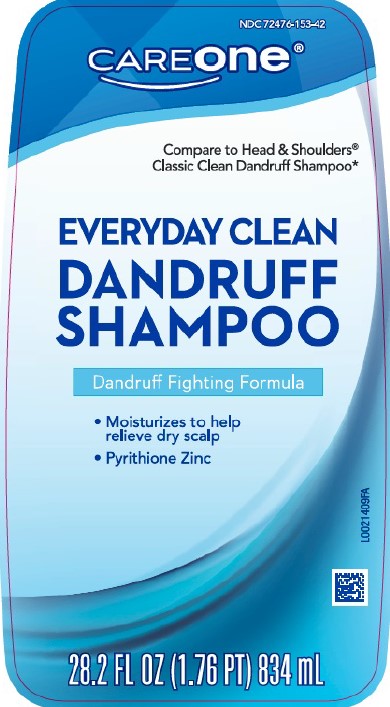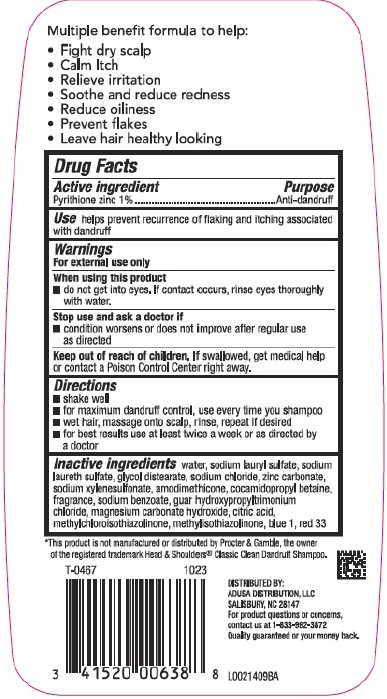 DRUG LABEL: Everyday Clean Dandruff
NDC: 72476-153 | Form: SHAMPOO
Manufacturer: Retail Business Services, LLC
Category: otc | Type: HUMAN OTC DRUG LABEL
Date: 20260206

ACTIVE INGREDIENTS: PYRITHIONE ZINC 10 mg/1 mL
INACTIVE INGREDIENTS: COCAMIDOPROPYL BETAINE; SODIUM BENZOATE; GUAR HYDROXYPROPYLTRIMONIUM CHLORIDE (1.7 SUBSTITUENTS PER SACCHARIDE); WATER; SODIUM LAURYL SULFATE; SODIUM LAURETH SULFATE; GLYCOL DISTEARATE; SODIUM CHLORIDE; ZINC CARBONATE; SODIUM XYLENESULFONATE; AMODIMETHICONE (800 CST); MAGNESIUM CARBONATE HYDROXIDE; CITRIC ACID MONOHYDRATE; METHYLCHLOROISOTHIAZOLINONE; METHYLISOTHIAZOLINONE; FD&C BLUE NO. 1; D&C RED NO. 33

Care One 153.008/153AZ rev 1, BA, BC, BD
Everyday Clean Dandruff Shampoo

Claims

Multiple benefit formula to help:

- Fight dry scalp
- Calm Itch
- Relieve irritation
- Soothe and reduce redness
- Reduce oiliness
- Prevent flakes
- Leave hair healthy looking

Active ingredient

Pyrithione zinc 1%

Purpose

Anti-dandruff

Use

Helps prevent recurrence or flaking and itching associated with dandruff

Warnings

for external use only

When using this product

- do not get into eyes. If contact occurs, rinse eyes thoroughly with water.

Stop use and ask a doctor if

- condition worsens or does not improve after regular use as directed

Keep out of each of children.

If swallowed, get medical help or contact a Poison Control Center right away.

Directions

- shake well
- for maximum dandruff control, use every time you shampoo
- wet hair, massage onto scalp, rinse, repeat if desired
- for best results use at least twice a week or as directed by a doctor

Inactive ingredients

water, sodium lauryl sulfate, sodium laureth sulfate, glycol distearate, sodium chloride, zinc carbonate, sodium xylenesulfonate, amodimethicone, cocamidopropyl betaine, fragrance, sodium benzoate, guar hydroxypropyltrimonium chloride, magnesium carbonate hydroxide, citric acid, methylchloroisothiazolinone, methylisothiazolinone, blue 1, red 33

Disclaimer

*This product is not manufactured or distributed by Procter & Gamble, the owner of the registered trademark Head & ShouldersClassic Clean Dandruff Shampoo.

Adverse reactions

DISTRIBUTED BY:

ADUSA DISTRIBUTION, LLC

SALISBURY, NC 28147

For product questions or concerns, contact us at 1-833-992-3872

Quality guaranteed or your money back.

principal display panel

NDC 71476-153-42

CAREone®

Compare to Head & Shoulders®Classic Clean Dandruff Shampoo*

EVERYDAY CLEAN

DANDRUFF

SHAMPOO

Dandruff Fighting Formula

- Moisturizes to help relieve dry scalp
- Pyrithione Zinc

28.2 FL OZ (1.76 PT) 834 mL